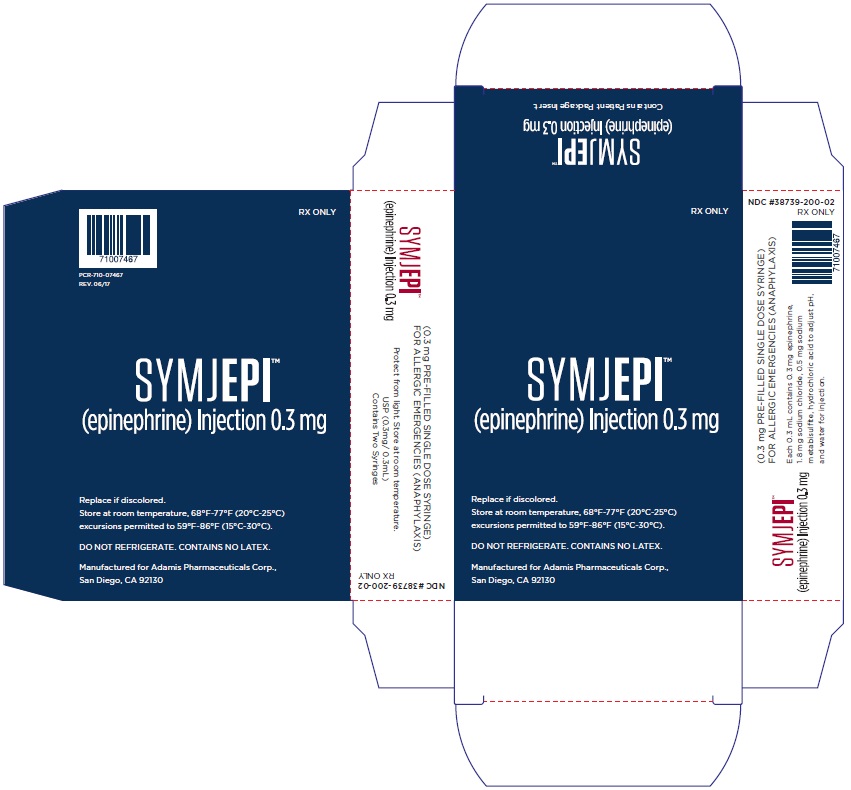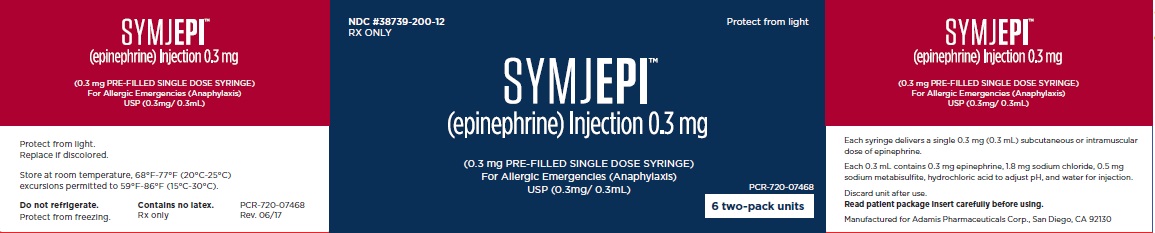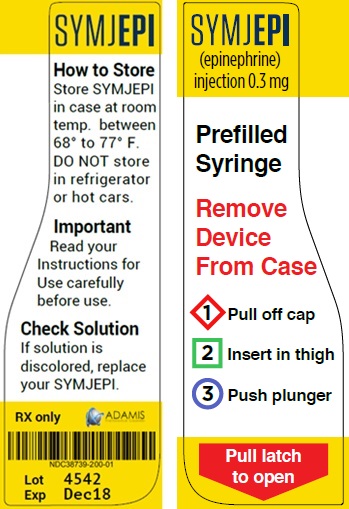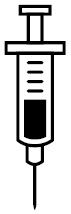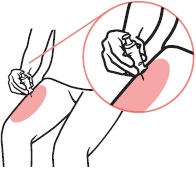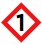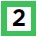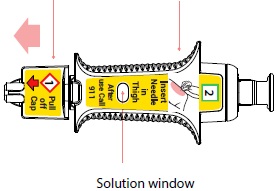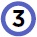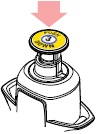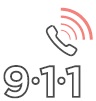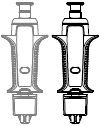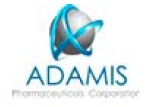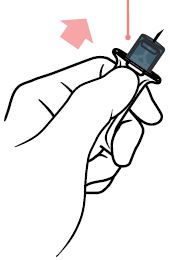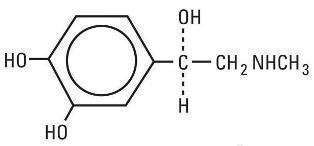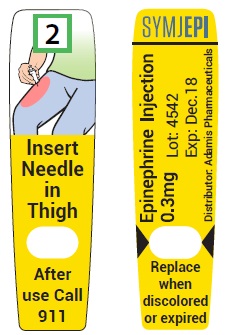 DRUG LABEL: SYMJEPI
NDC: 38739-200 | Form: INJECTION
Manufacturer: Adamis Pharmaceuticals Corporation
Category: prescription | Type: HUMAN PRESCRIPTION DRUG LABEL
Date: 20190206

ACTIVE INGREDIENTS: epinephrine 0.3 mg/0.3 mL
INACTIVE INGREDIENTS: sodium chloride 1.8 mg/0.3 mL; sodium metabisulfite 0.5 mg/0.3 mL; hydrochloric acid ; water

HIGHLIGHTS OF PRESCRIBING INFORMATION

These highlights do not include all the information needed to use SYMJEPI™ safely and effectively. See full prescribing information for SYMJEPI™.
SYMJEPI™ (epinephrine) injection, for intramuscular or subcutaneous use
Initial U.S. Approval: 1939

1 INDICATIONS AND USAGE

SYMJEPI contains epinephrine, a non-selective alpha and beta-adrenergic receptor agonist, indicated in the emergency treatment of allergic reactions (Type I) including anaphylaxis.

2 DOSAGE AND ADMINISTRATION

Patients greater than or equal to 30 kg (66 lbs): Inject SYMJEPI intramuscularly or subcutaneously into the anterolateral aspect of the thigh, through clothing if necessary. Each pre-filled syringe is for a single injection.

3 DOSAGE FORMS AND STRENGTHS

Injection: single-dose, pre-filled syringe for manual injection containing 0.3 mg/0.3 mL epinephrine sterile solution for injection, USP

4 CONTRAINDICATIONS

None.

5 WARNINGS AND PRECAUTIONS

- In conjunction with use, seek immediate medical or hospital care. (5.1)
- Do not inject intravenously, into buttock, or into digits, hands or feet. (5.2)
- To minimize the risk of injection-related injury, instruct caregivers to hold the child's leg firmly in place and limit movement prior to and during injection when administering to young children. (5.2)
- Rare cases of serious skin and soft tissue infections have been reported following epinephrine injection. Advise patients to seek medical care if they develop signs or symptoms of infection at the epinephrine injection site. (5.3)
- The presence of a sulfite in this product should not deter use. (5.4)
- Administer with caution in patients with heart disease; may aggravate angina pectoris or produce ventricular arrhythmias. (5.5)

6 ADVERSE REACTIONS

- Adverse reactions to epinephrine include anxiety, apprehensiveness, restlessness, tremor, weakness, dizziness, sweating, palpitations, pallor, nausea and vomiting, headache, and/or respiratory difficulties. (6)

To report SUSPECTED ADVERSE REACTIONS, contact Adamis Pharmaceuticals Corporation at 1-858-997-2400 or FDA at 1-800-FDA-1088 or www.fda.gov/medwatch.

7 DRUG INTERACTIONS

- Cardiac glycosides or diuretics: observe for development of cardiac arrhythmias. (7)
- Tricyclic antidepressants, monoamine oxidase inhibitors, levothyroxine sodium, and certain antihistamines: potentiate effects of epinephrine. (7)
- Beta-adrenergic blocking drugs: antagonize cardiostimulating and bronchodilating effects of epinephrine. (7)
- Alpha-adrenergic blocking drugs: antagonize vasoconstricting and hypertensive effects of epinephrine. (7)
- Ergot alkaloids: may reverse the pressor effects of epinephrine. (7)

8 USE IN SPECIFIC POPULATIONS

Elderly patients may be at greater risk of developing adverse reactions. (5.5, 8.5)

FULL PRESCRIBING INFORMATION

1 INDICATIONS AND USAGE

SYMJEPI is indicated in the emergency treatment of allergic reactions (Type I) including anaphylaxis to stinging insects (e.g., order Hymenoptera, which include bees, wasps, hornets, yellow jackets and fire ants) and biting insects (e.g., triatoma, mosquitoes), allergen immunotherapy, foods, drugs, diagnostic testing substances (e.g., radiocontrast media) and other allergens, as well as idiopathic anaphylaxis or exercise-induced anaphylaxis.

SYMJEPI is intended for immediate administration in patients who are determined to be at increased risk for anaphylaxis, including individuals with a history of anaphylactic reactions.

Anaphylactic reactions may occur within minutes after exposure and consist of flushing, apprehension, syncope, tachycardia, thready or unobtainable pulse associated with a fall in blood pressure, convulsions, vomiting, diarrhea and abdominal cramps, involuntary voiding, wheezing, dyspnea due to laryngeal spasm, pruritus, rashes, urticaria or angioedema.

SYMJEPI is intended for immediate administration as emergency supportive therapy only and is not a substitute for immediate medical care.

2 DOSAGE AND ADMINISTRATION

This product delivers 0.3 mg epinephrine injection (0.3 mL) and is intended for patients who weigh 30 kg or more (approximately 66 pounds or more).

Inject SYMJEPI intramuscularly or subcutaneously into the anterolateral aspect of the thigh with the needle facing downwards. It can be injected through clothing if necessary. Instruct caregivers of young children who are prescribed SYMJEPI and who may be uncooperative and kick or move during an injection to hold the leg firmly in place and limit movement prior to and during an injection [see Warnings and Precautions (5.2)].

Each SYMJEPI contains a single dose of epinephrine for single-use injection. Since the doses of Epinephrine delivered from SYMJEPI are fixed, consider using other forms of injectable epinephrine if doses lower than 0.3 mg are deemed necessary.

The prescriber should carefully assess each patient to determine the most appropriate dose of epinephrine, recognizing the life-threatening nature of the reactions for which this drug is indicated. With severe persistent anaphylaxis, repeat injections with an additional SYMJEPI may be necessary. More than two sequential doses of epinephrine should only be administered under direct medical supervision [see Warnings and Precautions (5.1)].

SYMJEPI prescribers should ensure that the patient or caregiver is instructed and understands the indications and use of this product. A health care provider should review the patient instructions for SYMJEPI, in detail, with the patient or caregiver. Patients and/or any other person who might be in a position to administer an epinephrine injection should be advised of the proper site for injection and given appropriate instructions about imbedding the needle before transferring the thumb to the syringe plunger [see Instructions for Use].

The epinephrine solution in the syringe should be inspected visually for particulate matter and discoloration. Epinephrine is light sensitive and should be stored in the outer case provided to protect it from light [see How Supplied/Storage and Handling (16.2)].

3 DOSAGE FORMS AND STRENGTHS

Injection: Single-dose pre-filled syringe for manual injection, containing 0.3 mg/0.3 mL epinephrine sterile solution for injection, USP

4 CONTRAINDICATIONS

None.

5 WARNINGS AND PRECAUTIONS

5.1 Emergency Treatment

SYMJEPI is intended for immediate administration as emergency supportive therapy and is not intended as a substitute for immediate medical care. In conjunction with the administration of epinephrine, the patient should seek immediate medical or hospital care. More than two sequential doses of epinephrine should only be administered under direct medical supervision [see Indications and Usage (1), Dosage and Administration (2) and Patient Counseling Information (17)].

5.2 Injection-related Complications

SYMJEPI should only be injected into the anterolateral aspect of the thigh [see Dosage and Administration (2) and Patient Counseling Information (17)].

- Do not inject intravenously. Large doses or accidental intravenous injection of epinephrine may result in cerebral hemorrhage due to sharp rise in blood pressure. Rapidly acting vasodilators can counteract the marked pressor effects of epinephrine if there is such inadvertent administration.
- Do not inject into buttock. Injection into the buttock may not provide effective treatment of anaphylaxis. Advise the patient to go immediately to the nearest emergency room for further treatment of anaphylaxis. Additionally, injection into the buttock has been associated with gas gangrene. Cleansing with alcohol does not kill bacterial spores and therefore, does not lower the risk.
- Do not inject into digits, hands or feet. Since epinephrine is a strong vasoconstrictor, accidental injection into the digits, hands or feet may result in loss of blood flow to the affected area. Advise the patient to go immediately to the nearest emergency room and to inform the healthcare provider in the emergency room of the location of the accidental injection. Treatment of such inadvertent administration should consist of vasodilation, in addition to further appropriate treatment of anaphylaxis [see Adverse Reactions (6)].
- Hold leg firmly during injection. To minimize the risk of injection related injury when administering SYMJEPI to young children, instruct caregivers to hold child's leg firmly in place and limit movement prior to and during injection.

5.3 Serious Infections at the Injection Site

Rare cases of serious skin and soft tissue infections, including necrotizing fasciitis and myonecrosis caused by Clostridia (gas gangrene), have been reported at the injection site following epinephrine injection for anaphylaxis. Clostridium spores can be present on the skin and introduced into the deep tissue with subcutaneous or intramuscular injection. While cleansing with alcohol may reduce presence of bacteria on the skin, alcohol cleansing does not kill Clostridium spores. To decrease the risk of Clostridium infection, do not inject SYMJEPI into the buttock [see Warnings and Precautions (5.2)]. Advise patients to seek medical care if they develop signs or symptoms of infection, such as persistent redness, warmth, swelling, or tenderness, at the epinephrine injection site.

5.4 Allergic Reactions Associated with Sulfite

The presence of a sulfite in this product should not deter administration of the drug for the treatment of serious allergic or other emergency situations even if the patient is sulfite-sensitive.

Epinephrine is the preferred treatment for serious allergic reactions or other emergency situations even though this product contains sodium metabisulfite, a sulfite that may, in other products, cause allergic-type reactions including anaphylactic symptoms or life threatening or less severe asthmatic episodes in certain susceptible persons.

The alternatives to using epinephrine in a life-threatening situation may not be satisfactory.

5.5 Disease Interactions

Some patients may be at greater risk for developing adverse reactions after epinephrine administration. Despite these concerns, it should be recognized that the presence of these conditions is not a contraindication to epinephrine administration in an acute, life-threatening situation. Therefore, patients with these conditions, and/or any other person who might be in a position to administer SYMJEPI to a patient experiencing anaphylaxis should be carefully instructed in regard to the circumstances under which epinephrine should be used.

- Patients with Heart Disease: Epinephrine should be administered with caution to patients who have heart disease, including patients with cardiac arrhythmias, coronary artery or organic heart disease, or hypertension. In such patients, or in patients who are on drugs that may sensitize the heart to arrhythmias, epinephrine may precipitate or aggravate angina pectoris as well as produce ventricular arrhythmias [see Drug Interactions (7) and Adverse Reactions (6)].
- Other Patients and Diseases: Epinephrine should be administered with caution to patients with hyperthyroidism, diabetes, elderly individuals, and pregnant women. Patients with Parkinson's disease may notice a temporary worsening of symptoms.

6 ADVERSE REACTIONS

Due to the lack of randomized, controlled clinical trials of epinephrine for the treatment of anaphylaxis, the true incidence of adverse reactions associated with the systemic use of epinephrine is difficult to determine. Adverse reactions reported in observational trials, case reports and studies are listed below. Common adverse reactions to systemically administered epinephrine include: anxiety; apprehensiveness; restlessness; tremor; weakness; dizziness; sweating; palpitations; pallor; nausea and vomiting; headache; and/or respiratory difficulties. These symptoms occur in some persons receiving therapeutic doses of epinephrine, but are more likely to occur in patients with hypertension or hyperthyroidism [see Warnings and Precautions (5.5)].

Arrhythmias, including fatal ventricular fibrillation, have been reported, particularly in patients with underlying cardiac disease or those receiving certain drugs [see Warnings and Precautions (5.5) and Drug Interactions (7)].

Rapid rises in blood pressure have produced cerebral hemorrhage, particularly in elderly patients with cardiovascular disease [see Warnings and Precautions (5.5)].

Angina may occur in patients with coronary artery disease [see Warnings and Precautions (5.5)].

Rare cases of stress cardiomyopathy have been reported in patients treated with epinephrine.

Accidental injection into the digits, hands or feet may result in loss of blood flow to the affected area [see Warnings and Precautions (5.2)].

Adverse events experienced as a result of accidental injections may include increased heart rate, local reactions including injection site pallor, coldness and hypoesthesia or injury at the injection site resulting in bruising, bleeding, discoloration, erythema or skeletal injury.

Injection into the buttock has resulted in cases of gas gangrene [see Warnings and Precautions (5.2)].

Rare cases of serious skin and soft tissue infections, including necrotizing fasciitis and myonecrosis caused by Clostridia (gas gangrene), have been reported at the injection site following epinephrine injection in the thigh [see Warnings and Precautions (5.2)].

7 DRUG INTERACTIONS

Patients who receive epinephrine while concomitantly taking cardiac glycosides, diuretics, or anti-arrhythmics should be observed carefully for the development of cardiac arrhythmias [see Warnings and Precautions (5.4)].

The effects of epinephrine may be potentiated by tricyclic antidepressants, monoamine oxidase inhibitors, levothyroxine sodium, and certain antihistamines, notably chlorpheniramine, tripelennamine, and diphenhydramine.

The cardiostimulating and bronchodilating effects of epinephrine are antagonized by beta-adrenergic blocking drugs, such as propranolol.

The vasoconstricting and hypertensive effects of epinephrine are antagonized by alpha-adrenergic blocking drugs, such as phentolamine.

Ergot alkaloids may also reverse the pressor effects of epinephrine.

8 USE IN SPECIFIC POPULATIONS

8.1 Pregnancy

Risk Summary

There are no adequate and well controlled studies of the acute effect of epinephrine in pregnant women. In animal reproductive studies, epinephrine administered by the subcutaneous route to rabbits, mice, and hamsters during the period of organogenesis was teratogenic at doses 7 times and higher than the maximum recommended human intramuscular and subcutaneous dose on a mg/m^2 basis. Epinephrine is the first-line medication of choice for the treatment of anaphylaxis during pregnancy in humans. Epinephrine should be used for treatment of anaphylaxis during pregnancy in the same manner as it is used in non-pregnant patients.

In the U.S. general population, the estimated background risks of major birth defects and miscarriage in clinically recognized pregnancies is 2-4% and of miscarriage is 15-20%, respectively.

Clinical Considerations

Disease-associated maternal and embryo/fetal risk:

During pregnancy, anaphylaxis can be catastrophic and can lead to hypoxic-ischemic encephalopathy and permanent central nervous system damage or death in the mother and, more commonly, in the fetus or neonate. The prevalence of anaphylaxis occurring during pregnancy is reported to be approximately 3 cases per 100,000 deliveries.

Management of anaphylaxis during pregnancy is similar to management in the general population. Epinephrine is the first line-medication of choice for treatment of anaphylaxis; it should be used in the same manner in pregnant and non-pregnant patients. In conjunction with the administration of epinephrine, the patient should seek immediate medical or hospital care.

Data

Animal Data

In an embryofetal development study with rabbits dosed during the period of organogenesis, epinephrine was shown to be teratogenic (including gastroschisis and embryonic lethality) at doses approximately 40 times the maximum recommended intramuscular or subcutaneous dose (on a mg/m^2 basis at a maternal subcutaneous dose of 1.2 mg/kg/day for two to three days).

In an embryofetal development study with mice dosed during the period of organogenesis, epinephrine was shown to be teratogenic (including embryonic lethality) at doses approximately 8 times the maximum recommended intramuscular or subcutaneous dose (on a mg/m^2 basis at maternal subcutaneous dose of 1 mg/kg/day for 10 days). These effects were not seen in mice at approximately 4 times the maximum recommended daily intramuscular or subcutaneous dose (on a mg/m^2 basis at a subcutaneous maternal dose of 0.5 mg/kg/day for 10 days).

In an embryofetal development study with hamsters dosed during the period of organogenesis from gestation days 7 to 10, epinephrine was shown to be teratogenic at doses approximately 7 times the maximum recommended intramuscular or subcutaneous dose (on a mg/m^2 basis at a maternal subcutaneous dose of 0.5 mg/kg/day).

8.2 Lactation

Risk Summary

There is no information regarding the presence of epinephrine in human milk, the effects on breastfed infants, or the effects on milk production. Epinephrine is the first line-medication of choice for treatment of anaphylaxis; it should be used in the same manner in breastfeeding and non-breastfeeding patients.

8.4 Pediatric Use

SYMJEPI may be given safely to pediatric patients at a dosage appropriate to body weight [see Dosage and Administration (2)]. Clinical experience with the use of epinephrine suggests that the adverse reactions seen in children are similar in nature and extent to those both expected and reported in adults. Since the dose of epinephrine delivered from SYMJEPI is fixed, consider using other forms of injectable epinephrine if a dose lower than 0.3 mg is deemed necessary.

8.5 Geriatric Use

Clinical studies for the treatment of anaphylaxis have not been performed in subjects aged 65 and over to determine whether they respond differently from younger subjects. However, other reported clinical experience with use of epinephrine for the treatment of anaphylaxis has identified that geriatric patients may be particularly sensitive to the effects of epinephrine. Therefore, SYMJEPI should be administered with caution in elderly individuals, who may be at greater risk for developing adverse reactions after epinephrine administration. [see Warnings and Precautions (5.4), Overdosage (10)].

10 OVERDOSAGE

Overdosage of epinephrine may produce extremely elevated arterial pressure, which may result in cerebrovascular hemorrhage, particularly in elderly patients. Overdosage may also result in pulmonary edema because of peripheral vascular constriction together with cardiac stimulation. Treatment consists of rapidly acting vasodilators or alpha-adrenergic blocking drugs and/or respiratory support.

Epinephrine overdosage can also cause transient bradycardia followed by tachycardia, and these may be accompanied by potentially fatal cardiac arrhythmias. Premature ventricular contractions may appear within one minute after injection and may be followed by multifocal ventricular tachycardia (prefibrillation rhythm). Subsidence of the ventricular effects may be followed by atrial tachycardia and occasionally by atrioventricular block. Treatment of arrhythmias consists of administration of a beta-adrenergic blocking drug such as propranolol.

Overdosage sometimes results in extreme pallor and coldness of the skin, metabolic acidosis, and kidney failure. Suitable corrective measures must be taken in such situations.

11 DESCRIPTION

Each SYMJEPI pre-filled, syringe delivers a single dose of 0.3 mg of epinephrine from epinephrine injection, USP (0.3mg/0.3 mL).

Each SYMJEPI (epinephrine injection, USP) syringe contains 0.8 mL of sterile aqueous solution of epinephrine for intramuscular or subcutaneous administration. The syringe is overfilled for stability purposes; more than half of the solution remains in the syringe after use and CANNOT BE REUSED.

Each 0.3 mL contains 0.3 mg epinephrine, 1.8 mg sodium chloride, 0.5 mg sodium metabisulfite, hydrochloric acid to adjust pH, and Water for Injection. The pH range is 2.2-5.0.

Epinephrine is a sympathomimetic catecholamine (a non-selective alpha and beta-adrenergic receptor agonist) designated chemically as (-)-3,4-Dihydroxy-α-[(methylamino)methyl]benzyl alcohol and has the following structure:

The molecular weight of epinephrine is 183.20.

Epinephrine solution deteriorates rapidly on exposure to air or light, turning pink from oxidation to adrenochrome and brown from formation of melanin. Replace SYMJEPI if the solution appears discolored (pinkish or brown color), cloudy, or contains particles.

12 CLINICAL PHARMACOLOGY

12.1 Mechanism of Action

Epinephrine acts on both alpha and beta-adrenergic receptors.

12.2 Pharmacodynamics

Through its action on alpha-adrenergic receptors, epinephrine lessens the vasodilation and increased vascular permeability that occurs during anaphylaxis, which can lead to loss of intravascular fluid volume and hypotension.

Through its action on beta-adrenergic receptors, epinephrine causes bronchial smooth muscle relaxation and helps alleviate bronchospasm, wheezing and dyspnea that may occur during anaphylaxis.

Epinephrine also alleviates pruritus, urticaria, and angioedema and may relieve gastrointestinal and genitourinary symptoms associated with anaphylaxis because of its relaxer effects on the smooth muscle of the stomach, intestine, uterus and urinary bladder.

When given subcutaneously or intramuscularly, epinephrine has a rapid onset and short duration of action.

13 NONCLINICAL TOXICOLOGY

13.1 Carcinogenesis, Mutagenesis, Impairment of Fertility

Long-term studies to evaluate the carcinogenic potential of epinephrine have not been conducted.

Epinephrine and other catecholamines have been shown to have mutagenic potential in vitro. Epinephrine was positive in the Salmonella bacterial reverse mutation assay, positive in the mouse lymphoma assay, and negative in the in vivo micronucleus assay. Epinephrine is an oxidative mutagen based on the E. coli WP2 Mutoxitest bacterial reverse mutation assay. This should not prevent the use of epinephrine under the conditions noted under Indications and Usage (1).

The potential for epinephrine to impair reproductive performance has not been evaluated, but epinephrine has been shown to decrease implantation in female rabbits dosed subcutaneously with 1.2 mg/kg/day (40-fold the highest human intramuscular or subcutaneous daily dose) during gestation days 3 to 9.

16 HOW SUPPLIED/STORAGE AND HANDLING

16.1 How Supplied

SYMJEPI (epinephrine injection, USP) 0.3 mg pre-filled syringes are available as a single pack, NDC 38739-200-01 containing a single pre-filled syringe, and as a two-pack, NDC 38739-200-02, a pack that contains 2 pre-filled syringes.

16.2 Storage and Handling

Protect from light. Epinephrine is light sensitive and should be stored in the case provided to protect it from light. Store at 20° to 25°C (68° to 77°F); excursions permitted to 15° to 30°C (59° to 86°F) (See USP Controlled Room Temperature). Do not refrigerate. Before using, check to make sure the solution in the syringe is clear and colorless. Replace the product if the solution is discolored (pinkish or brown color), cloudy, or contains particles. Used SYMJEPI should be given to a healthcare provider or emergency room personnel for proper disposal. Expired or discolored SYMJEPI should be returned to a healthcare provider or pharmacy for proper disposal.

17 PATIENT COUNSELING INFORMATION

[see FDA-Approved Patient Labeling (Patient Information and Instructions for Use)]

A healthcare provider should review the patient instructions and operation of SYMJEPI, in detail, with the patient or caregiver.

Epinephrine is essential for the treatment of anaphylaxis. Patients who are at risk of or have a history of severe allergic reactions (anaphylaxis) to insect stings or bites, foods, drugs, and other allergens, as well as idiopathic and exercise-induced anaphylaxis, should be carefully instructed about the circumstances under which epinephrine should be used.

Administration and Training

Instruct patients and/or caregivers in the appropriate use of SYMJEPI. SYMJEPI should be injected into the middle of the outer thigh (through clothing, if necessary). Each syringe is for a single-use injection. Advise patients to seek immediate medical care in conjunction with administration of SYMJEPI.

Young children may be uncooperative and kick or move during and injection. Instruct caregivers of young children who are prescribed SYMJEPI to hold the leg firmly in place and limit movement prior to and during an injection [see Warnings and Precautions (5.2)].

Complete patient information, including dosage, directions for proper administration and precautions can be found inside each SYMJEPI carton. A printed label on the surface of the SYMJEPI case shows instructions for use.

Adverse Reactions

Epinephrine may produce symptoms and signs that include an increase in heart rate, the sensation of a more forceful heartbeat, palpitations, sweating, nausea and vomiting, difficulty breathing, pallor, dizziness, weakness or shakiness, headache, apprehension, nervousness, or anxiety. These signs and symptoms usually subside rapidly, especially with rest, quiet and recumbency. Patients with hypertension or hyperthyroidism may develop more severe or persistent effects, and patients with coronary artery disease could experience angina. Patients with diabetes may develop increased blood glucose levels following epinephrine administration. Patients with Parkinson’s disease may notice a temporary worsening of symptoms. [see Warnings and Precautions (5.5)].

Accidental Injection

Advise patients to seek immediate medical care in the case of accidental injection. Since epinephrine is a strong vasoconstrictor when injected into the digits, hands, or feet, treatment should be directed at vasodilatation if there is such an accidental injection to these areas [see Warnings and Precautions (5.2)].

Serious Infections at the Injection Site

Rare cases of serious skin and soft tissue infections, including necrotizing fasciitis and myonecrosis caused by Clostridia (gas gangrene), have been reported at the injection site following epinephrine injection for anaphylaxis. Advise patients to seek medical care if they develop signs or symptoms of infection, such as persistent redness, warmth, swelling, or tenderness, at the epinephrine injection site [see Warnings and Precautions (5.3)].

Storage and Handling

Instruct patients to inspect the epinephrine solution visually periodically. SYMJEPI should be replaced if the epinephrine solution appears discolored (pinkish or brown color), cloudy, or contains particles. Epinephrine is light sensitive and should be stored in the outer case provided to protect it from light. Instruct patients that SYMJEPI must be used or properly disposed once the protective cap covering the needle is removed [see How Supplied/Storage and Handling (16.2)]. Instruct patients to give a used SYMJEPI syringe to their healthcare provider or emergency room personnel for proper disposal, and to return expired or discolored SYMJEPI to their healthcare provider or pharmacy for proper disposal.

Complete patient information, including dosage, directions for proper administration and precautions can be found inside each SYMJEPI case.

Manufactured for Adamis Pharmaceuticals Corporation. San Diego, CA

PATIENT INFORMATION

SYMJEPI™ (sim-JEP-ee)
(epinephrine)
injection for intramuscular or subcutaneous use
For allergic emergencies (anaphylaxis)

Read this Patient Information leaflet carefully before using SYMJEPI and each time you get a refill. There may be new information. You, your parent, caregiver, or others who may be in a position to administer SYMJEPI should know how to use it before you have an allergic emergency. This information does not take the place of talking with your healthcare provider about your medical condition or your treatment.

What is the most important information I should know about SYMJEPI?

1. SYMJEPI contains epinephrine, a medicine used to treat allergic emergencies (anaphylaxis). Anaphylaxis can be life threatening, can happen within minutes, and can be caused by stinging and biting insects, allergy injections, foods, medicines, exercise, or unknown causes. Symptoms of anaphylaxis may include:

- trouble breathing
- wheezing
- hoarseness (changes in the way your voice sounds)
- hives (raised reddened rash that may itch)
- severe itching
- swelling of your face, lips, mouth, or tongue
- skin rash, redness, or swelling
- fast heartbeat
- weak pulse
- feeling very anxious
- confusion
- stomach pain
- losing control of urine or bowel movements (incontinence)
- diarrhea or stomach cramps
- dizziness, fainting, or “passing out” (unconsciousness)

2. Always carry your SYMJEPI with you because you may not know when anaphylaxis may happen.
Talk to your healthcare provider if you need additional prefilled syringes to keep at work, school, or other locations. Tell your family members, caregivers, and others where you keep your SYMJEPI and how to use it before you need it. You may be unable to speak in an allergic emergency.

3. When you have an allergic emergency (anaphylaxis)

- Use SYMJEPI right away.
- Get emergency medical help right away. You may need further medical attention. You may need to use a second SYMJEPI if symptoms continue or recur. Only a healthcare provider should give additional doses of epinephrine if you need more than 2 injections for a single anaphylaxis episode.

What is SYMJEPI?

- SYMJEPI is a disposable, prefilled syringe used to treat life-threatening, allergic emergencies including anaphylaxis in people who are at risk for or have a history of serious allergic emergencies. Each prefilled syringe contains a single (1 time) dose of epinephrine.
- SYMJEPI is for immediate self (or caregiver) administration and does not take the place of emergency medical care. You should get emergency help right away after using SYMJEPI.
- SYMJEPI is for people who have been prescribed this medicine by their healthcare provider.
- The SYMJEPI prefilled syringe (0.3 mg) is for patients who weigh 66 pounds or more (30 kilograms or more).
- It is not known if the SYMJEPI prefilled syringe (0.3 mg) is safe and effective in patients who weigh less than 66 pounds (30 kilograms).

Before using SYMJEPI, tell your healthcare provider about all of your medical conditions, including if you:

- have heart problems or high blood pressure.
- have diabetes.
- have thyroid problems.
- have asthma.
- have a history of depression.
- have Parkinson’s disease.
- are pregnant or plan to become pregnant. It is not known if epinephrine will harm your unborn baby.
- are breastfeeding or plan to breastfeed. It is not known if epinephrine passes into your breast milk.

Tell your healthcare provider about all the medicines you take, including prescription and over-the-counter medicines, vitamins, and herbal supplements. Tell your healthcare provider of all known allergies.

Especially tell your healthcare provider if you take certain asthma medicines.

SYMJEPI and other medicines may affect each other, causing side effects. SYMJEPI may affect the way other medicines work, and other medicines may affect how SYMJEPI works.

Know the medicines you take. Keep a list of them to show your healthcare provider and pharmacist when you get a new medicine.

Use your SYMJEPI for treatment of anaphylaxis as prescribed by your healthcare provider, regardless of your medical conditions or the medicines you take.

How should I use SYMJEPI?

- Each SYMJEPI prefilled syringe contains only 1 dose of medicine.
- SYMJEPI should be injected into the middle of your outer thigh (upper leg) with the needle facing downwards. It can be injected through your clothing if needed.
- Read the Instructions for Use at the end of this Patient Information leaflet about the right way to use SYMJEPI.
- Your healthcare provider will show you how to safely use the SYMJEPI prefilled syringe.
- Use SYMJEPI exactly as your healthcare provider tells you to use it.
- If you inject a young child with SYMJEPI, hold their leg firmly in place before and during the injection to prevent injuries. Ask your healthcare provider to show you how to properly hold the leg of a young child during injection.
- You may need to use a second SYMJEPI if symptoms continue or recur. Only a healthcare provider should give additional doses of epinephrine if you need more than 2 injections for a single anaphylaxis episode.
- Caution: Never put your thumb, fingers, or hand over the exposed needle. Accidental injection of epinephrine into the finger, hands or feet may cause a loss of blood flow to these areas. If this happens, go immediately to the nearest emergency room. Tell the healthcare provider where on your body you received the accidental injection.
- Always carry your SYMJEPI with you in case of an allergic emergency. Additional instructional materials and information are available at www.symjepi.com.
- Do not drop the carrier case or SYMJEPI prefilled syringe. If the carrier case or prefilled syringe is dropped, check for damage and leakage. Dispose of the prefilled syringe and carrier case, and replace if damage or leakage is noticed or suspected.

What are the possible side effects of SYMJEPI?

SYMJEPI may cause serious side effects.

- SYMJEPI should only be injected into the middle of your outer thigh (upper leg). Do not inject SYMJEPI into your:
  - veins
  - buttocks
  - fingers, toes, hands, or feet

If you accidentally inject SYMJEPI into any other part of your body, go to the nearest emergency room right away. Tell the healthcare provider where on your body you received the accidental injection.

- Rarely, patients who have used SYMJEPI may develop infections at the injection site within a few days of an injection. Some of these infections can be serious. Call your healthcare provider right away if you have any of the following at an injection site:
  - redness that does not go away
  - swelling
  - tenderness
  - the area feels warm to the touch
- Cuts on the skin, bent needles, and needles that remain in the skin after the injection, have happened in young children who do not cooperate and kick or move during an injection. If you inject a young child with SYMJEPI, hold their leg firmly in place before and during the injection to prevent injuries. Ask your healthcare provider to show you how to properly hold the leg of a young child during injection.
- If you have certain medical conditions, or take certain medicines, your condition may get worse or you may have longer lasting side effects when you use your SYMJEPI. Talk to your healthcare provider about all your medical conditions.

Common side effects of SYMJEPI include:

- fast, irregular or “pounding” heartbeat
- sweating
- headache
- weakness
- shakiness
- paleness
- feelings of over excitement, nervousness or anxiety
- dizziness
- nausea and vomiting
- breathing problems

These side effects may go away with rest. Tell your healthcare provider if you have any side effect that bothers you or that does not go away.

These are not all the possible side effects of SYMJEPI. For more information, ask your healthcare provider or pharmacist.

Call your doctor for medical advice about side effects. You may report side effects to FDA at 1-800-FDA-1088.

How should I store SYMJEPI?

- Store SYMJEPI at room temperature between 68°F to 77°F (20°C to 25°C).
- Protect from light.
- Do not expose to extreme cold or heat. For example, do not store in your vehicle’s glove box and do not store in the refrigerator or freezer.
- Examine the contents in the clear window of your prefilled syringe periodically. The solution should be clear. If the solution is discolored (pinkish or brown color), is cloudy, or contains solid particles, replace the unit.
- Always keep your SYMJEPI prefilled syringe in the carrier case to protect it from damage. The carrier case is not waterproof.
- The needle cap helps to prevent accidental injection. Do not remove the needle cap until you need to use SYMJEPI.
- Your SYMJEPI has an expiration date. Replace it before the expiration date.

Keep SYMJEPI and all medicines out of the reach of children.

General information about the safe and effective use of SYMJEPI.

Medicines are sometimes prescribed for purposes other than those listed in a Patient Information Leaflet. Do not use SYMJEPI for a condition for which it was not prescribed. Do not give your SYMJEPI to other people.

This Patient Information leaflet summarizes the most important information about SYMJEPI. If you would like more information, talk to your healthcare provider. You can ask your pharmacist or healthcare provider for information about SYMJEPI that is written for health professionals.

What are the ingredients in SYMJEPI?

Active Ingredients: epinephrine
Inactive Ingredients: sodium chloride, sodium metabisulfite, hydrochloric acid, and water.

Manufactured for Adamis Pharmaceuticals Corporation. San Diego, CA
SYMJEPI is a registered trademark of Adamis Pharmaceuticals Corporation.
For more information and instructions on the use of SYMJEPI, go to www.symjepi.com or call 1-858-997-2400.

Important Information

- Your prefilled syringe is designed to work through clothing.
- The needle cap on the SYMJEPI prefilled syringe helps to prevent needle sticks and accidental injection of epinephrine. Do not remove the needle cap until you are ready to use it.
- Only inject into the middle of the outer thigh (upper leg). Never inject into any other part of the body.
- Never put your thumb, fingers, or your hand over the exposed needle.
- If an accidental injection happens, get medical help right away.
- Do not place patient information or any other foreign objects in the carrier case with the prefilled syringe, as this may prevent you from removing the prefilled syringe for use.

This Patient Information has been approved by the U.S. Food and Drug Administration Issued: 06/2017.

INSTRUCTIONS FOR USE

SYMJEPI (sim-JEP-ee) (epinephrine injection, USP) 0.3 mg prefilled syringe

For Allergic Emergencies (anaphylaxis)

Read this Instructions for Use carefully before you use this product.

Before you need to use your SYMJEPI syringe make sure your healthcare provider shows you the right way to use it. Parents, caregivers, and others who may be in a position to administer SYMJEPI should also understand how to use it. If you have questions, ask your healthcare provider.

Get Ready to Use SYMJEPI

SYMJEPI works like a standard prefilled syringe.

SYMJEPI is injected downwards, into the thigh, while sitting (as shown), through clothing if necessary.

Ready to Use SYMJEPI

When ready to inject, pull off cap to expose needle.

DO NOT put finger on top of the device.

If you are administering SYMJEPI to a young child, hold the leg firmly in place while administering the injection.

Hold SYMJEPI by finger grips only and slowly insert the needle into the thigh.

After needle is in thigh: Push the plunger all the way down until it clicks and hold for 2 seconds.

Remove the syringe and massage the injection area for 10 seconds.

Get Help

Get emergency medical help now.

Tell healthcare provider that you received an injection of epinephrine.

Use second syringe if necessary

You may need a second SYMJEPI syringe if symptoms continue or recur.

SYMJEPI is a single use prefilled syringe that delivers a fixed dose of epinephrine. The prefilled syringe cannot be reused. It is normal for most of the medicine to remain in the syringe after the dose has been injected.

The correct dose has been injected if the plunger has been pushed all the way down and the solution window is at least partially blocked.

If you will be administering SYMJEPI to a young child, ask your healthcare provider to show you how to properly hold the leg in place while administering a dose.

After use and Disposal — Hold SYMJEPI with one hand with your fingers behind the needle and slide the safety guard over the needle until it clicks. Put the used syringe into the grey case and close the case.

- Take the case with the used syringe with you when you go to see a healthcare provider.
- Tell the healthcare provider that you have received an injection of epinephrine. Show the healthcare provider where you received the injection.
- Give your used SYMJEPI syringe to your healthcare provider for inspection and proper disposal.

After Use

Safety Guard

Using one hand with fingers behind the needle slide safety guard over needle.

For more information see Patient Information sheet or ask your healthcare provider.

How to Store — Keep SYMJEPI in its plastic case nearby and ready for use at all times.

- Store at room temperature, between 68°F to 77°F (20°C to 25°C). Do not expose to extreme cold or heat. For example do not store in your vehicle's glove box and do not store in the refrigeration or freezer.
- Store the SYMJEPI syringe in its closed plastic case to protect from light.

Check Your SYMJEPI Periodically — The solution should be clear when viewed through the window on the device. If the solution is discolored (pinkish or brown color), cloudy or contains particles, replace the SYMJEPI with a new one.

Your SYMJEPI Has an Expiration Date — Example Dec 18 = December 31, 2018. Replace SYMJEPI before the expiration date. Dispose of expired SYMJEPI properly by taking the SYMJEPI in its case to a healthcare provider or hospital emergency room.

For more information about SYMJEPI prefilled syringe and proper use of the product, call 1-858-997-2400 or visit www.symjepi.com.

This Instructions for Use has been approved by the U.S. Food and Drug Administration.

SYMJEPI is a registered trademark of Adamis Pharmaceuticals Corporation.

Manufactured for Adamis Pharmaceuticals, San Diego, CA 92130, USA. Approved: June 2017

SYMJEPI

(epinephrine injection, USP) 0.3 mg pre-filled syringe

Instructions for Use

Pull out and Read before Use

Rx Only

PRINCIPAL DISPLAY PANEL

Syringe Label

SYMJEPI

Epinephrine Injection

0.3 mg

Lot: Exp:

Distributor: Adamis Pharmaceuticals

Replace when discolored or expired

[2] Insert Needle in Thigh

After use Call 911

Syringe Case Label

SYMJEPI
(epinephrine)
injection 0.3 mg

Prefilled Syringe

Remove Device From Case

1 Pull off cap
2 Insert in thigh
3 Push plunger

Pull latch to open

How to Store
Store SYMJEPI in case at room temp. between 68° to 77°F. DO NOT store in refrigerator or hot cars.

Important
Read your Instructions for Use carefully before use.

Check Solution

If solution is discolored, replace your SYMJEPI.

RX only

ADAMIS Pharmaceutical Corporation

NDC 38739-200-01

Lot

Exp

2-Pack Inner Carton

NDC #38739-200-02

RX ONLY

SYMJEPITM

(epinephrine) Injection 0.3 mg

(0.3 mg PRE-FILLED SINGLE DOSE SYRINGE)

FOR ALLERGIC EMERGENCIES (ANAPHYLAXIS)

Protect from light. Store at room temperature.

USP (0.3mg/ 0.3mL)

Contains Two Syringes

2-Pack Outer Carton

NDC #38739-200-12

RX ONLY

Protect from light

SYMJEPITM

(epinephrine) Injection 0.3 mg

(0.3 mg PRE-FILLED SINGLE DOSE SYRINGE)

For Allergic Emergencies (Anaphylaxis)

USP (0.3mg/ 0.3mL)

PCR-720-07468

6 two-pack units